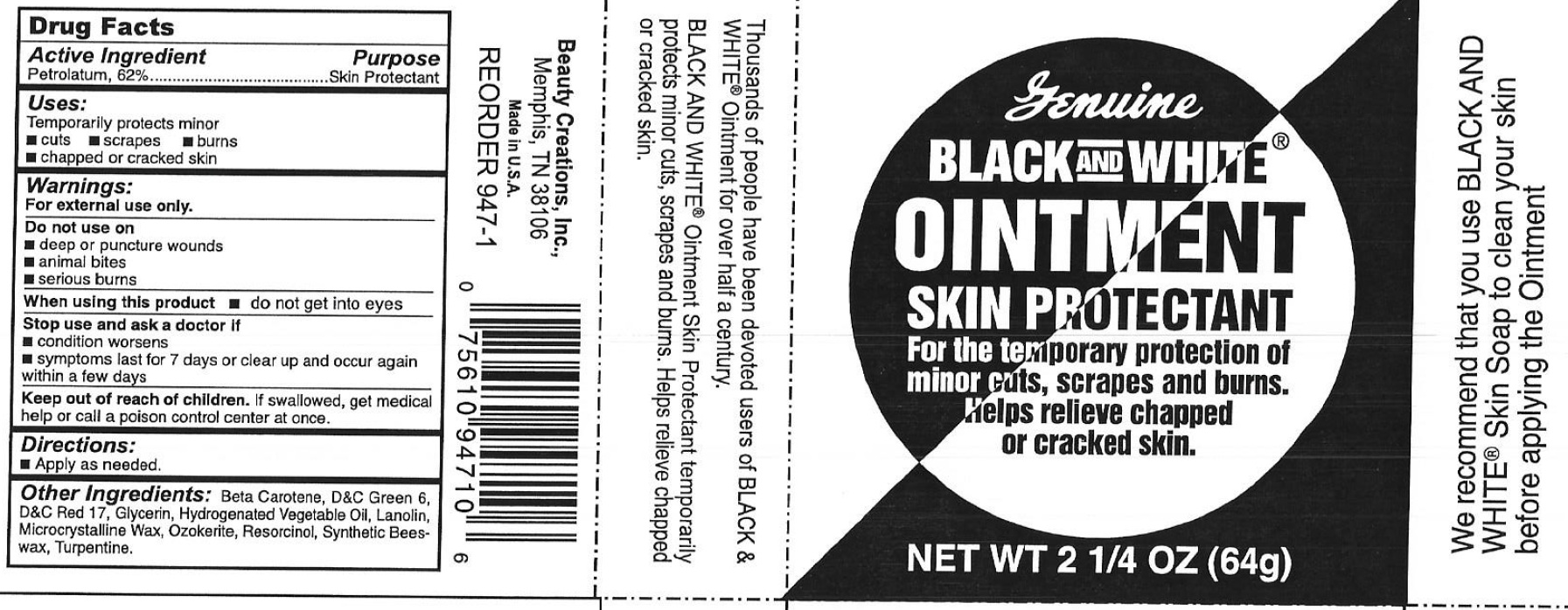 DRUG LABEL: Black and White Skin Protectant
NDC: 12022-004 | Form: OINTMENT
Manufacturer: J. Strickland & Co.
Category: otc | Type: HUMAN OTC DRUG LABEL
Date: 20231021

ACTIVE INGREDIENTS: PETROLATUM 620 mg/1 g
INACTIVE INGREDIENTS: .BETA.-CAROTENE; GLYCERIN; LANOLIN; MICROCRYSTALLINE WAX; CERESIN; RESORCINOL; TURPENTINE

Black & White Skin Protectant Ointment

Active Ingredients:

Petrolatum, 62%

Purpose

Skin Protectant

Uses:

Temporarily protects minor

- cuts
- scrapes
- burns
- chapped or cracked skin

Warnings:

For External Use Only.

Do not use on

- deep or puncture wounds
- animal bites
- serious burns

When using this product

- do not get into eyes

Stop use and ask a doctor if

- condition worsens
- symptoms last for 7 days or clear up and occur again within a few days

Keep out of reach of children.

- If swallowed, get medical help or call a poison control center at once.

Directions:

- Apply as needed.

Other Ingredients:

Beta Carotene, D&C Green 6, D&C Red 17, Glycerin, Hydrogenated Vegetable Oil, Lanolin, Microcrystalline Wax, Ozokerite, Resorcinol, Synthetic Bees-wax, Turpentine.